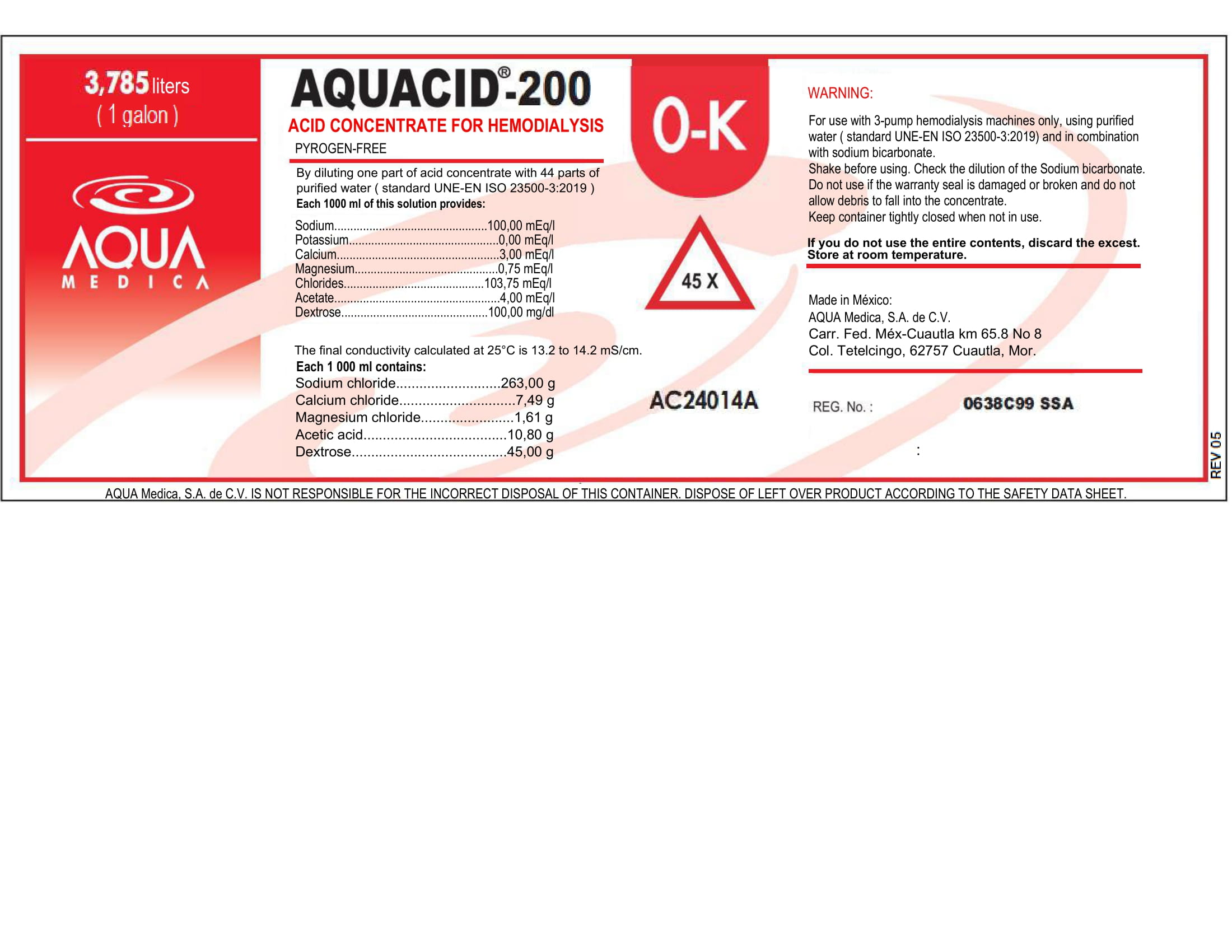 DRUG LABEL: AQUACID-200
NDC: 81943-603 | Form: SOLUTION, CONCENTRATE
Manufacturer: Aqua Medica, S.A. de C.V.
Category: otc | Type: HUMAN OTC DRUG LABEL
Date: 20251110

ACTIVE INGREDIENTS: POTASSIUM CHLORATE 0.671 g/100 mL
INACTIVE INGREDIENTS: SODIUM CHLORIDE 26.3 g/100 mL; ACETIC ACID C-11 1.08 g/100 mL; DEXTROSE 4.5 g/100 mL; WATER; MAGNESIUM CHLORIDE 0.161 g/100 mL; CALCIUM CHLORIDE 0.749 g/100 mL

This is a Hemodialysis Acid Concentrate, Pyrogen-Free.

By diluiting one part of this acid concentrate with 44 parts of purified water (ISO Standard 13959:2014), each 1000 ml of this solucion provides:

Sodium: 100.00 mEq/l

Potassium: 0.00 mEq/l

Calcium: 3.00 mEq/l

Magnesium: 0.75 mEq/l

Chlorides: 103.75 mEq/l

Acetate: 4.00 mEq/l

Dextrose: 100.00 mEq/l

The final conductivity calculated at 25 C is 13.2 to 14.2 mS/cm.

Active Ingredient(s)

Potassium Chloride

Purpose

For use with 3-pump hemodialysis machines only.

Use

For use with 3-pump hemodialysis machines only, using purified water (Standard 13959:2014) and in combination with sodium bicarbonate.

Warnings

For use with 3-pump hemodialysis machines only.

Do not use

- If the warranty seal is damaged or broken and do not allow debris to fall into the concentrate.

WHEN USING

Using purified water (Standard 13959:2014) and in combination with sodium bicarbonate.
Keep out of reach of children. If swallowed, get medical help or contact a Poison Control Center right away.

STOP USE

If you do not use the entire contents, discard the excess.

Keep out of reach of children. If swallowed, get medical help or contact a Poison Control Center right away.

Directions

- By diluting one part of this acid concentrate with 44 parts of purified water (ISO Standard 13959:2014).

Other information

- Store at room temperature.
- Keep container tightly closed when not in use.

Inactive ingredients

Sodium chloride, calcium chloride, acetic acid, dextrose, purified water USP

RECENT MAJOR CHANGES

For use with 3-pump hemodialysis machines only, using purified water (Standard 13959:2014) and in combination with sodium bicarbonate.

By diluting one part of this acid concentrate with 44 parts of purified water (ISO Standard 13959:2014).

Package Label - Principal Display Panel

3785 mL NDC: 81943-603-03